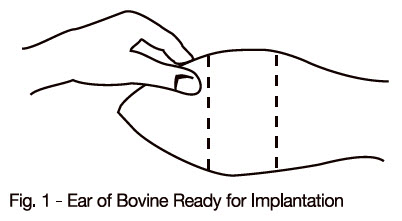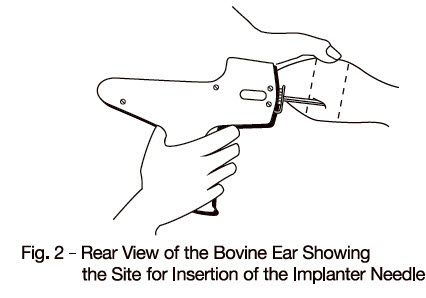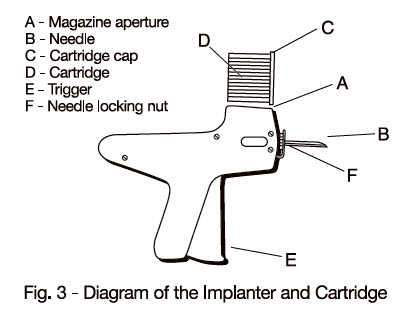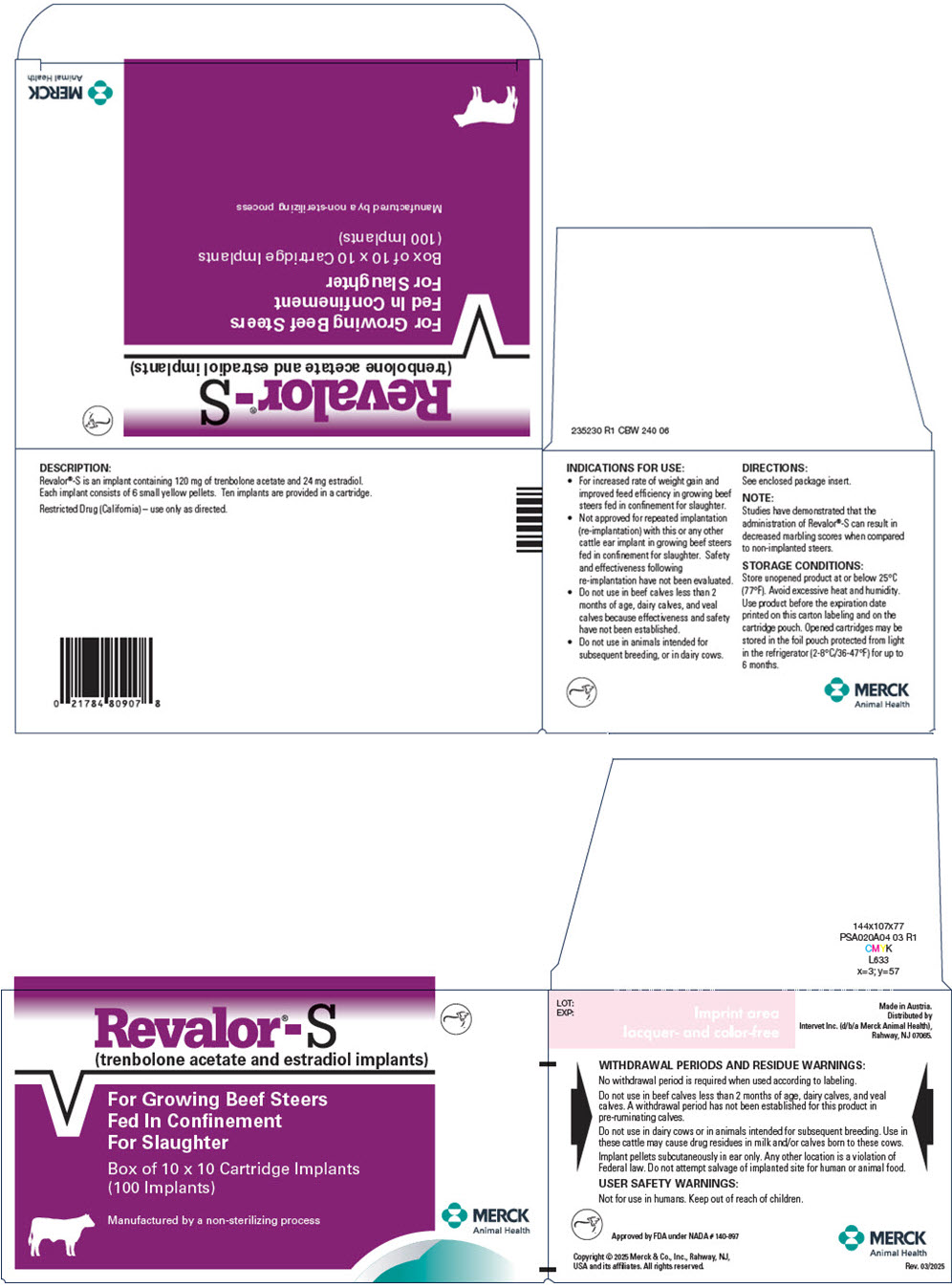 DRUG LABEL: Revalor-S
NDC: 57926-020 | Form: IMPLANT
Manufacturer: Merck Sharp & Dohme Corp.
Category: animal | Type: OTC ANIMAL DRUG LABEL
Date: 20250815

ACTIVE INGREDIENTS: TRENBOLONE ACETATE 120 mg/1 1; ESTRADIOL 24 mg/1 1

Revalor®-S
(trenbolone acetate and estradiol implants)

For Growing Beef Steers
Fed In Confinement
For Slaughter

DESCRIPTION:

Revalor®-S is an implant containing 120 mg of trenbolone acetate and 24 mg estradiol. Each implant consists of 6 small yellow pellets. Ten implants are provided in a cartridge.

Manufactured by a non-sterilizing process.

INDICATIONS FOR USE:

For increased rate of weight gain and improved feed efficiency in growing beef steers fed in confinement for slaughter.

Not approved for repeated implantation (re-implantation) with this or any other cattle ear implant in growing beef steers fed in confinement for slaughter. Safety and effectiveness following re-implantation have not been evaluated.

Do not use in beef calves less than 2 months of age, dairy calves, and veal calves because effectiveness and safety have not been established.

Do not use in animals intended for subsequent breeding, or in dairy cows.

NOTE:

Studies have demonstrated that the administration of Revalor®-S can result in decreased marbling scores when compared to non-implanted steers.

DIRECTIONS:

The cartridge is designed to be used with a special implanting tool. The special implanting tool is available from Intervet Inc. Ten doses (implants) are in each cartridge. The implant is placed under the skin on the posterior aspect of the ear (see SITE OF IMPLANTATION and METHOD OF USE sections).

See Page 2, DIRECTIONS for more detailed implantation directions.

With the animal suitably restrained, the skin on the outer surface of the ear should be cleaned. The implant is then administered by the method shown in the diagram below:

SITE OF IMPLANTATION:

After appropriately restraining the animal to allow access to the ear, cleanse the skin at the implant needle puncture site. It is subcutaneous between the skin and cartilage on the back side of the ear and below the midline of the ear. The implant must not be placed closer to the head than the edge of the cartilage ring farthest from the head. The location of insertion of the needle is a point toward the tip of the ear and at least a needle length away from the intended deposition site. Care should be taken to avoid injuring the major blood vessels or cartilage of the ear.

METHOD OF USE:

1. Do not remove the cap of the cartridge containing the implants.
2. Place the cartridge (D) with the capped end to the front into slot at the top of the implanter magazine marked (A) on the diagram.
3. Gently push the cartridge into the slot until it clicks into place.
4. The implanter is then ready for use.
5. Take the ear of the animal firmly with the free hand in the manner shown in Fig. 1. Then insert the needle into the subcutaneous tissue at the point indicated in Fig. 2.
6. After inserting the needle to its full extent, squeeze the trigger (E) gradually. Allow the pellets of the implant to be deposited in a single row.
7. Withdraw the implanter. This will advance the cartridge one groove in the magazine and the next implant is now ready for use.
8. When all the implants have been administered, the cartridge will discharge out the bottom of the magazine and may be replaced by a new one.
9. To change the needle, loosen the needle locking nut labeled (F) in Fig. 3 and replace the needle. Tighten the nut finger tight and the implanter is ready for use.

WITHDRAWAL PERIODS AND RESIDUE WARNINGS:

No withdrawal period is required when used according to labeling.

Do not use in beef calves less than 2 months of age, dairy calves, and veal calves. A withdrawal period has not been established for this product in pre-ruminating calves.

Do not use in dairy cows or in animals intended for subsequent breeding. Use in these cattle may cause drug residues in milk and/or calves born to these cows.

Implant pellets subcutaneously in ear only. Any other location is a violation of Federal law. Do not attempt salvage of implanted site for human or animal food.

USER SAFETY WARNINGS:

Not for use in humans. Keep out of reach of children.

STORAGE CONDITIONS:

Store unopened product at or below 25°C (77°F). Avoid excessive heat and humidity. Use product before the expiration date printed on the carton labeling and on the cartridge pouch. Opened cartridges may be stored in the foil pouch protected from light in the refrigerator (2-8°C/36-47°F) for up to 6 months.

HOW SUPPLIED:

Box of 10 cartridges, each containing 10 implants per cartridge (100 implants total).

QUESTIONS/COMMENTS?

For a copy of the Safety Data Sheet or to report side effects, contact Merck Animal Health Technical Services at 1-800-211-3573. For additional information about reporting side effects for animal drugs, contact FDA at 1-888-FDA-VETS or http://www.fda.gov/reportanimalae

Made in Austria.

Distributed by
Intervet Inc. (d/b/a Merck Animal Health),
Rahway, NJ 07065.

Copyright © 2025 Merck & Co., Inc., Rahway, NJ, USA and its affiliates. All rights reserved.

Restricted Drug (California) – use only as directed.

Approved by FDA under NADA # 140-897

Rev. 03/2025

235228 R2

PRINCIPAL DISPLAY PANEL - 10 x 10 Cartridge Implant Box

Revalor®-S
(trenbolone acetate and estradiol implants)

For Growing Beef Steers
Fed In Confinement
For Slaughter

Box of 10 x 10 Cartridge Implants
(100 Implants)

Manufactured by a non-sterilizing process

MERCK
Animal Health